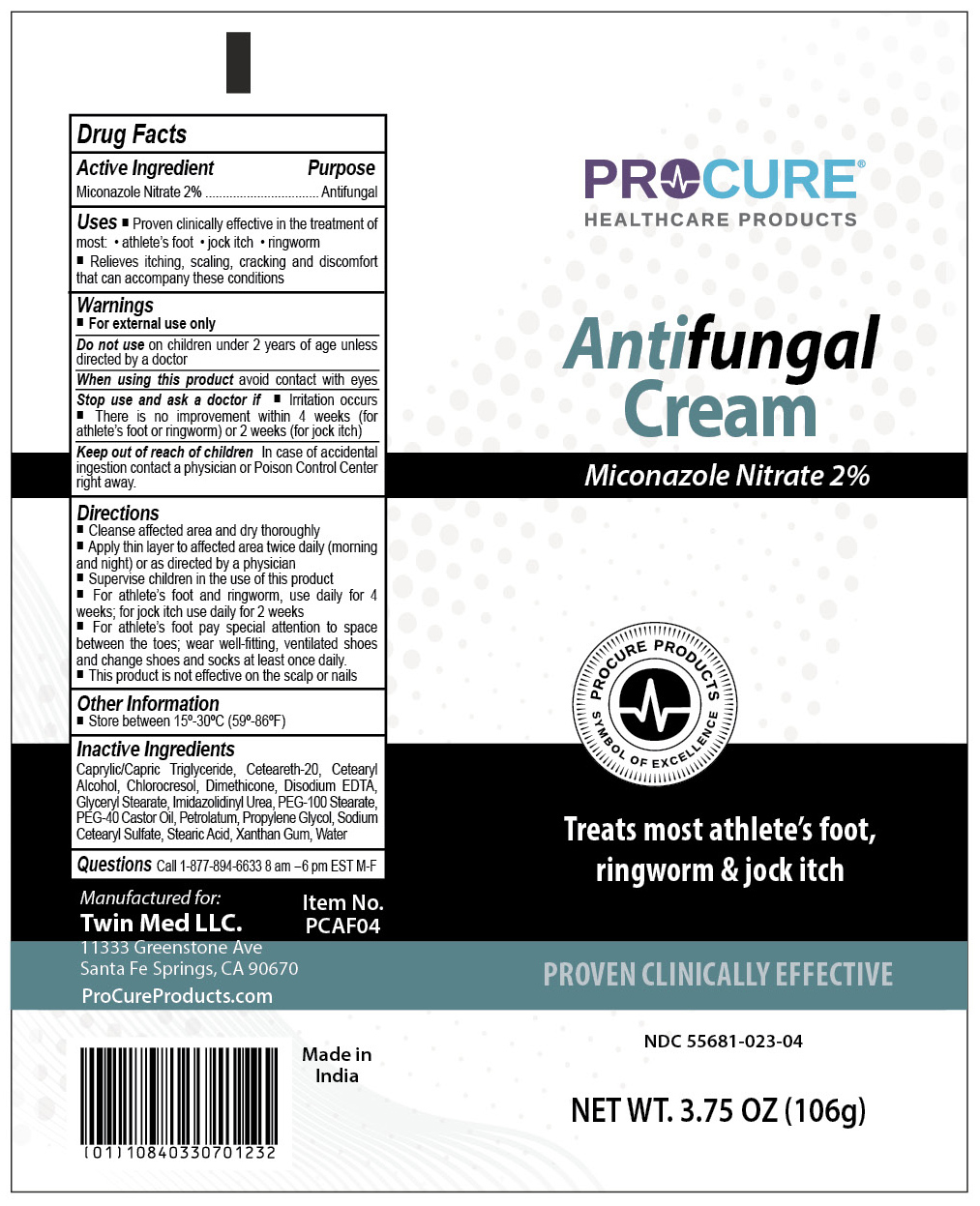 DRUG LABEL: ProCure Antifungal Cream
NDC: 55681-023 | Form: CREAM
Manufacturer: Twin Med LLC
Category: otc | Type: HUMAN OTC DRUG LABEL
Date: 20250713

ACTIVE INGREDIENTS: MICONAZOLE NITRATE 2 g/100 g
INACTIVE INGREDIENTS: EDETATE DISODIUM; IMIDAZOLIDINYL UREA; SODIUM CETEARYL SULFATE; CAPRYLIC/CAPRIC TRIGLYCERIDE; CETEARYL ALCOHOL; PEG-100 STEARATE; PROPYLENE GLYCOL; GLYCERYL STEARATE; STEARIC ACID; WATER; DIMETHICONE; CETEARETH-20; CHLOROCRESOL; PEG-40 CASTOR OIL; PETROLATUM; XANTHAN GUM

Active Ingredient

Miconazole Nitrate 2%

Purpose

Antifungal

Use

Uses

- Proven clinically effective in the treatment of most athlete's foot, jock itch and ringworm
- Relieves itching, scaling, cracking and discomfort that can accompany these conditions

Warnings

For external use only

Do not use on children under 2 years of age unless directed by a doctor

When using this product avoid contact with eyes

Stop using and ask a doctor if

- Irritation occurs
- There is no improvement within 4 weeks (for athlete’s foot or ringworm) or 2 weeks (for jock itch)

Keep out of reach of Children. In case of accidental ingestion, contact a physician or Poison Control Center right away.

Directions

- Cleanse affected area and dry thoroughly
- Apply thin layer to affected area twice daily (morning and night) or as directed by a physician
- Supervise children in the use of this product
- For athlete’s foot and ringworm, use daily for 4 weeks; for jock itch use daily for 2 weeks
- For athlete’s foot pay special attention to space between the toes; wear well-fitting, ventilated shoes and change shoes and socks at least once daily.
- This product is not effective on the scalp or nails

Inactive Ingredients

Caprylic/Capric Triglyceride, Ceteareth-20, Cetearyl Alcohol, Chlorocresol, Dimethicone, Disodium EDTA, Glyceryl Stearate, Imidazolidinyl Urea, PEG-100 Stearate, PEG-40 Castor Oil, Petrolatum, Propylene Glycol, Sodium Cetearyl Sulfate, Stearic Acid, Xanthan Gum, Water